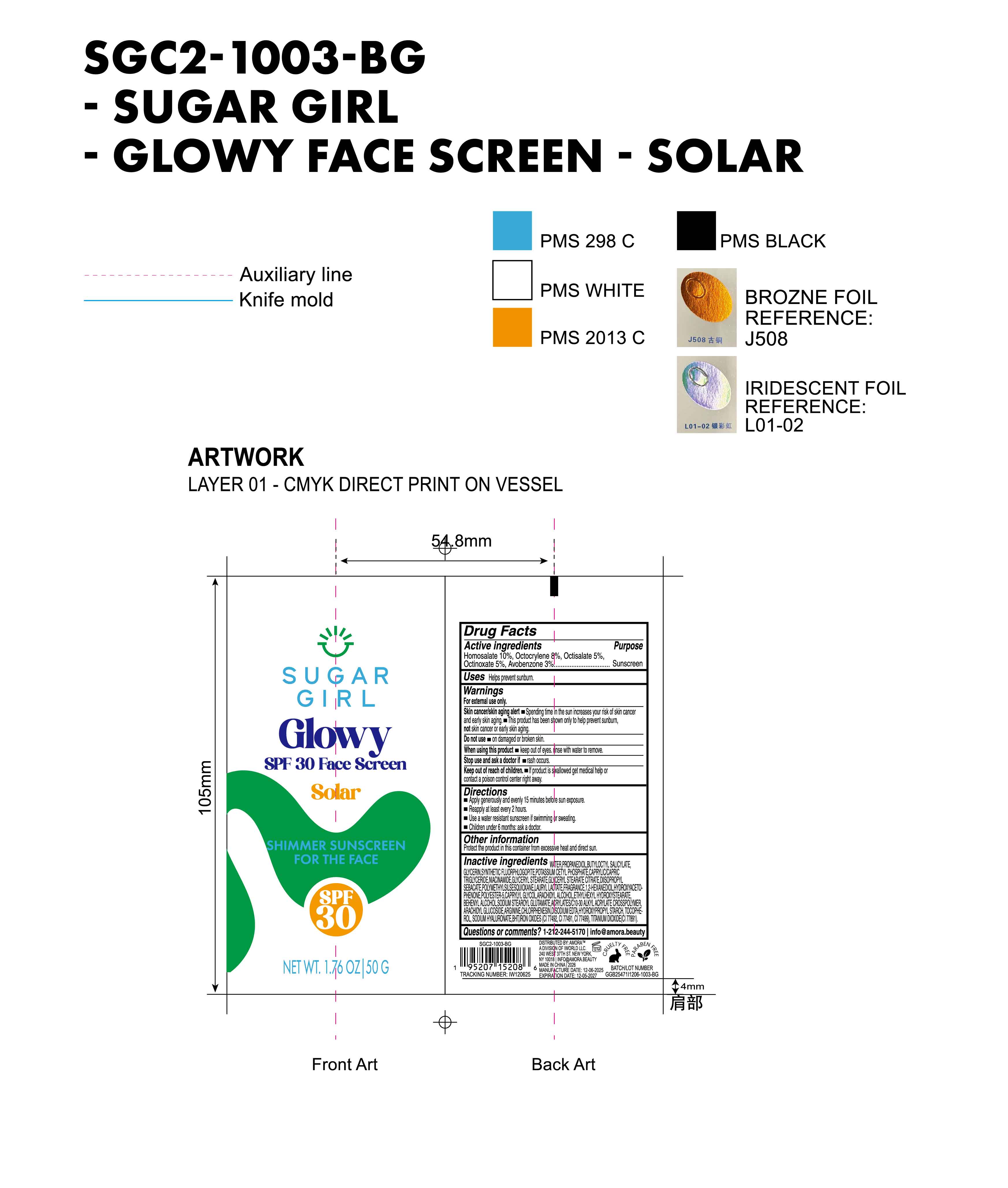 DRUG LABEL: Sugargirl Glowy SPF 30 Face Screen Solar Shimmer Sunscreen for the face
NDC: 85161-136 | Form: CREAM
Manufacturer: Longway Technology(Guangzhou)Co.,Ltd.
Category: otc | Type: HUMAN OTC DRUG LABEL
Date: 20251223

ACTIVE INGREDIENTS: OCTINOXATE 0.05 g/1 g; HOMOSALATE 0.1 g/1 g; OCTOCRYLENE 0.08 g/1 g; OCTISALATE 0.05 g/1 g; AVOBENZONE 0.03 g/1 g
INACTIVE INGREDIENTS: GLYCERYL STEARATE; BEHENYL ALCOHOL; SODIUM HYALURONATE; BHT; CHLORPHENESIN; MAGNESIUM POTASSIUM ALUMINOSILICATE FLUORIDE; POLYESTER-5 (TG-48); HYDROXYPROPYL STARCH; BUTYLOCTYL SALICYLATE; ARACHIDYL GLUCOSIDE; 1,2-HEXANEDIOL; ACRYLATES/C10-30 ALKYL ACRYLATE CROSSPOLYMER (60000 MPA.S); EDETATE DISODIUM; GLYCERYL STEARATE CITRATE; WATER; FRAGRANCE 13576; HYDROXYACETOPHENONE; CI 77491; DIISOPROPYL SEBACATE; LAURYL LACTATE; GLYCERIN; POTASSIUM CETYL PHOSPHATE; POLYMETHYLSILSESQUIOXANE (11 MICRONS); CI 77492; CI 77499; ARGININE; CAPRYLIC/CAPRIC TRIGLYCERIDE; CI 77891; ETHYLHEXYL HYDROXYSTEARATE; CAPRYLYL GLYCOL; TOCOPHEROL; NIACINAMIDE; PROPANEDIOL; ARACHIDYL ALCOHOL; SODIUM STEAROYL GLUTAMATE

INACTIVE INGREDIENT

WATER, PROPANEDIOL, BUTYLOCTYL SALICYLATE, GLYCERIN, SYNTHETIC FLUORPHLOGOPITE, POTASSIUM CETYL PHOSPHATE, CAPRYLIC/CAPRIC TRIGLYCERIDE, NIACINAMIDE,GLYCERYL STEARATE, GLYCERYL STEARATE CITRATE, DIISOPROPYL SEBACATE, POLYMETHYLSILSESQUIOXANE, LAURYL LACTATE, FRAGRANCE, 1,2-HEXANEDIOL, HYDROXYACETOPHENONE, POLYESTER-5, CAPRYLYL GLYCOL, ARACHIDYL ALCOHOL, ETHYLHEXYL HYDROXYSTEARATE, BEHENYL ALCOHOL,SODIUM STEAROYL GLUTAMATE, ACRYLATES/C10-30 ALKYL ACRYLATE CROSSPOLYMER, ARACHIDYL GLUCOSIDE, ARGININE, CHLORPHENESIN, DISODIUM EDTA, HYDROXYPROPYL STARCH, TOCOPHEROL, SODIUM HYALURONATE, CI 77492,CI 77491, 77499)TITANIUM DIOXIDE(CI 77891)

PURPOSE

Sunscreen

KEEP OUT OF REACH OF CHILDREN

If product is swallowed get medical help or contact a poison control center right away.

ACTIVE INGREDIENT

Homosalate 10%, Octocrylene 8%, Octisalate 5%, Octinoxate 5%, Avobenzone 3%

QUESTIONS

1-212-244-5170 info@amora.beauty

OTHER SAFETY INFORMATION

Protect the product in this container from excessive heat and direct sun.

DOSAGE AND ADMINISTRATION

Apply generously and evenly 15 minutes before sun exposure.

Reapply at least every 2 hours.

Use a water resistant sunscreen if swimming or sweating.

Children under 6 months: ask a doctor.

WARNINGS

For external use only

Skin cancer/skin aging alert

Spending time in the sun increases your risk of skin cancer and early skin aging.

This product has been shown only to help prevent sunburn,not skin cancer or early skin aging.

Do not use on damaged or broken skin.

When using this product keep out of eyes.rinse with water to remove.

Stop use and ask a doctor if rash occurs.

Keep out of reach of children. If product is swallowed get medical help or contact a poison control center right away.

INDICATIONS AND USAGE

Helps prevent sunburn.